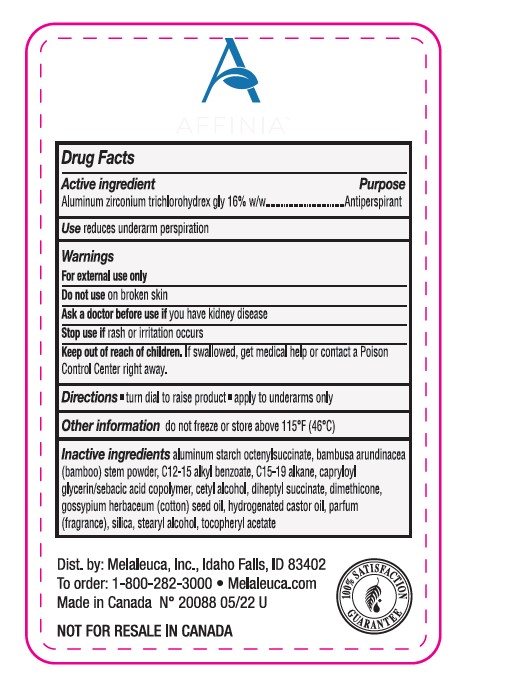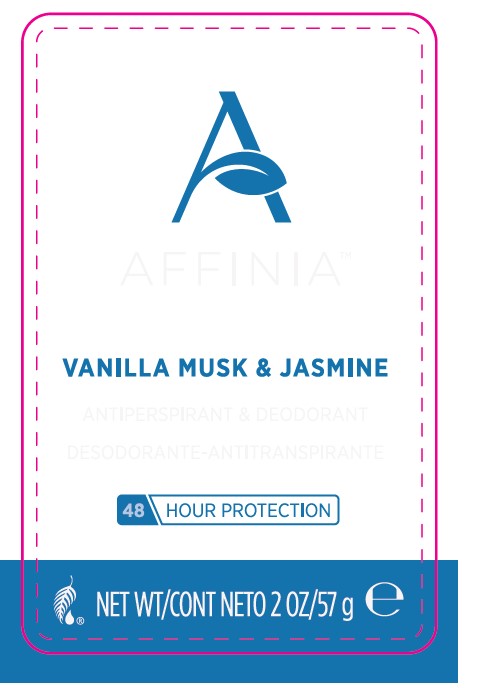 DRUG LABEL: Affinia Antiperspirant Deodorant
NDC: 54473-338 | Form: STICK
Manufacturer: Melaleuca, Inc.
Category: otc | Type: HUMAN OTC DRUG LABEL
Date: 20250122

ACTIVE INGREDIENTS: ALUMINUM ZIRCONIUM TETRACHLOROHYDREX GLY 16 g/57 g
INACTIVE INGREDIENTS: DIHEPTYL SUCCINATE; ALKYL (C12-15) BENZOATE; CETYL ALCOHOL; GOSSYPIUM HERBACEUM SEED RESIN; .ALPHA.-TOCOPHEROL ACETATE; CAPRYLOYL GLYCERIN/SEBACIC ACID COPOLYMER (2000 MPA.S); HYDROGENATED CASTOR OIL; DIMETHICONE 100; STEARYL ALCOHOL; C15-19 ALKANE; SILICON DIOXIDE; ALUMINUM STARCH OCTENYLSUCCINATE; BAMBUSA ARUNDINACEA STEM

Affinia Antiperspirant Deodorant Vanilla Musk and Jasmine